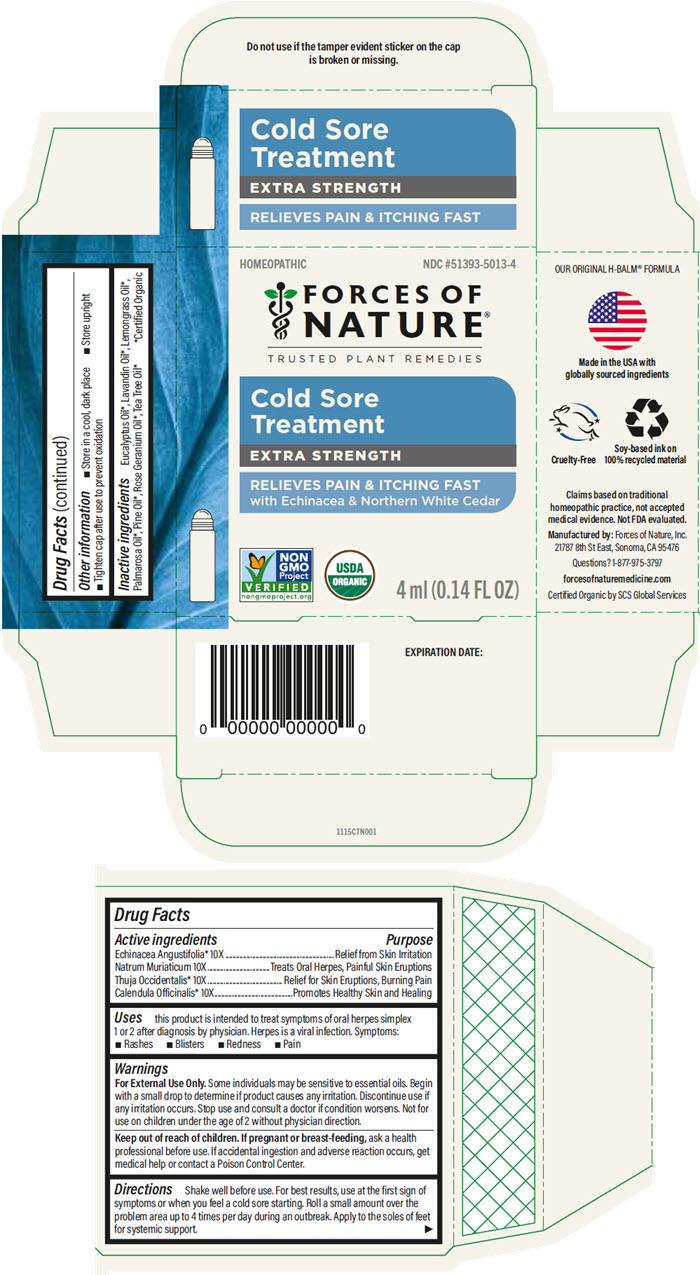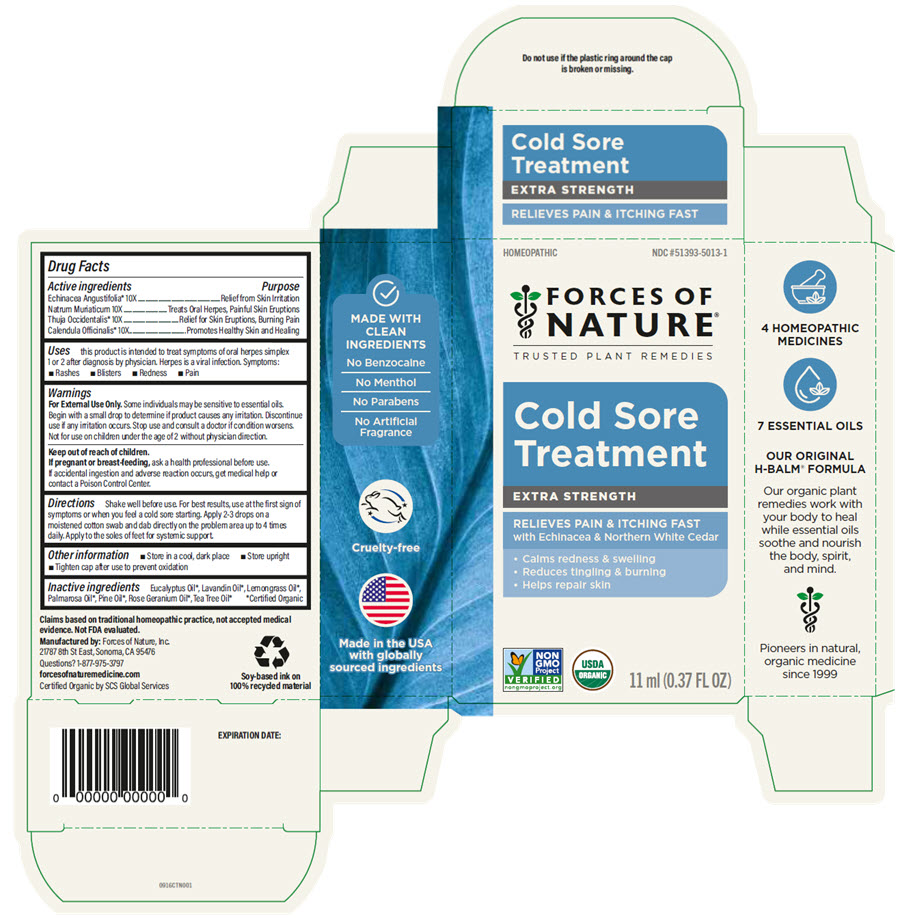 DRUG LABEL: Cold Sore Treatment 
NDC: 51393-5013 | Form: SOLUTION/ DROPS
Manufacturer: Forces of Nature
Category: homeopathic | Type: HUMAN OTC DRUG LABEL
Date: 20250822

ACTIVE INGREDIENTS: ECHINACEA ANGUSTIFOLIA WHOLE 10 [hp_X]/100 mL; SODIUM CHLORIDE 10 [hp_X]/100 mL; THUJA OCCIDENTALIS LEAFY TWIG 10 [hp_X]/100 mL; CALENDULA OFFICINALIS FLOWERING TOP 10 [hp_X]/100 mL
INACTIVE INGREDIENTS: EUCALYPTUS RADIATA FLOWERING TOP OIL; Lavandin Oil; WEST INDIAN LEMONGRASS OIL; Palmarosa Oil; PINE NEEDLE OIL (PINUS SYLVESTRIS); GERANIUM OIL, ALGERIAN TYPE; Tea Tree Oil

Cold Sore Treatment
Extra Strength

Drug Facts

ACTIVE INGREDIENT

Active ingredients | Purpose
Echinacea Angustifolia [Certified Organic] 10X | Relief from Skin Irritation
Natrum Muriaticum 10X | Treats Oral Herpes, Painful Skin Eruptions
Thuja Occidentalis 10X | Relief for Skin Eruptions, Buming Pain
Calendula Officinalis 10X | Promotes Healthy Skin and Healing

Uses

this product is intended to treat symptoms of oral herpes simplex 1 or 2 after diagnosis by physician. Herpes is a viral infection. Symptoms:

- Rashes
- Blisters
- Redness
- Pain

Warnings

For External Use Only. Some individuals may be sensitive to essential oils. Begin with a small drop to determine if product causes any irritation. Discontinue use if any irritation occurs. Stop use and consult a doctor if condition worsens. Not for use on children under the age of 2 without physician direction.

Keep out of reach of children. If pregnant or breast-feeding, ask a health professional before use. If accidental ingestion and adverse reaction occurs, get medical help or contact a Poison Control Center.

Directions

Shake well before use. For best results, use at the first sign of symptoms or when you feel a cold sore starting. Roll a small amount over the problem area up to 4 times per day during an outbreak. Apply to the soles of feet for systemic support.

Other information

- Store in a cool, dark place
- Store upright
- Tighten cap after use to prevent oxidation

Inactive ingredients

Eucalyptus Oil, Lavandin Oil, Lemongrass Oil, Palmarosa Oil, Pine Oil, Rose Geranium Oil, Tea Tree Oil

Questions?

1-877-975-3797

Manufactured by: Forces of Nature, Inc.
21787 8th St East, Sonoma, CA 95476

PRINCIPAL DISPLAY PANEL - 4 ml Bottle Carton

HOMEOPATHIC

NDC #51393-5013-4

FORCES OF
NATURE®
TRUSTED PLANT REMEDIES

Cold Sore
Treatment

EXTRA STRENGTH

RELIEVES PAIN & ITCHING FAST
with Echinacea & Northern White Cedar

NON
GMO
Project
VERIFIED
nongmoproject.org

USDA
ORGANIC

4 ml (0.14 FL OZ)

PRINCIPAL DISPLAY PANEL - 11 ml Bottle Carton

HOMEOPATHIC

NDC #51393-5013-1

FORCES OF
NATURE®
TRUSTED PLANT REMEDIES

Cold Sore
Treatment

EXTRA STRENGTH

RELIEVES PAIN & ITCHING FAST
with Echinacea & Northern White Cedar

- Calms redness & swelling
- Reduces tingling & burning
- Helps repair skin

NON
GMO
Project
VERIFIED
nongmoproject.org

USDA
ORGANIC

11 ml (0.37 FL OZ)